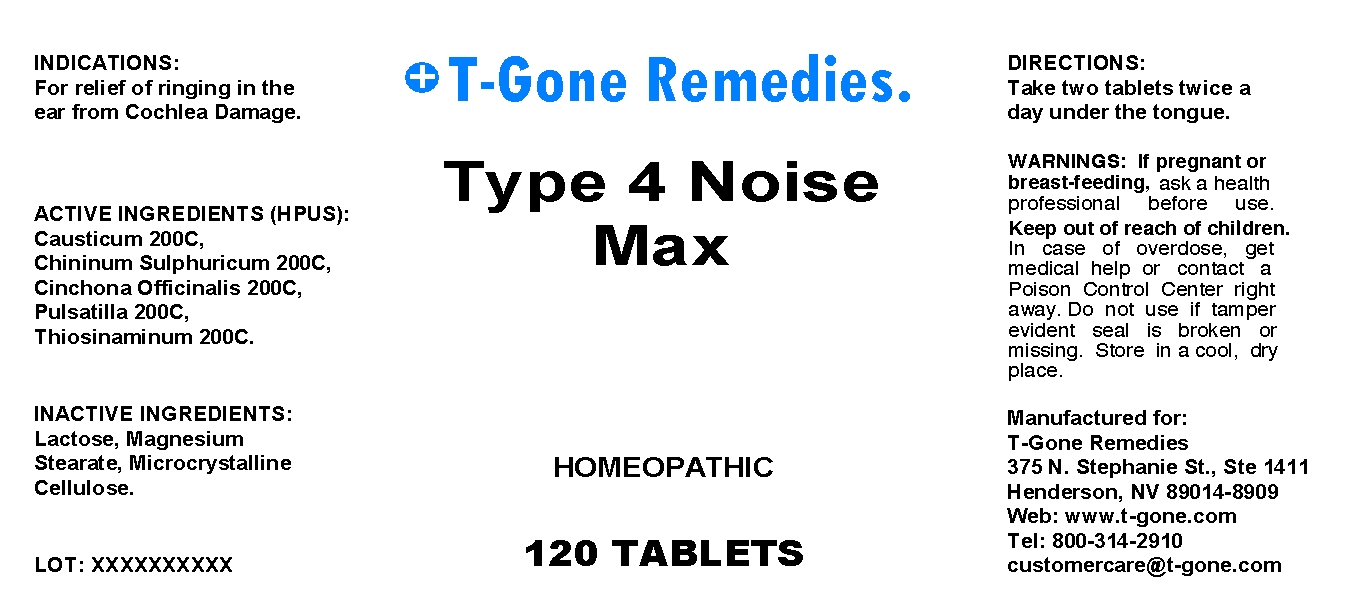 DRUG LABEL: Type 4 Noise Max
NDC: 57520-0428 | Form: TABLET
Manufacturer: Apotheca Company
Category: homeopathic | Type: HUMAN OTC DRUG LABEL
Date: 20100714

ACTIVE INGREDIENTS: CAUSTICUM 200 [hp_C]/1 mg; QUININE SULFATE 200 [hp_C]/1 mg; CINCHONA OFFICINALIS BARK 200 [hp_C]/1 mg; PULSATILLA VULGARIS 200 [hp_C]/1 mg; ALLYLTHIOUREA 200 [hp_C]/1 mg
INACTIVE INGREDIENTS: LACTOSE; MAGNESIUM STEARATE; CELLULOSE, MICROCRYSTALLINE

Type 4 Noise Max

ACTIVE INGREDIENT

ACTIVE INGREDIENTS: Causticum 200C, Chininum sulphuricum 200C, Cinchona officinalis 200C, Pulsatilla 200C, Thiosinaminum 200C.

PURPOSE

INDICATIONS: For relief of ringing in the ear from Cochlea Damage.

WARNINGS

WARNINGS: If pregnant or breast-feeding, ask a health professional before use.

Keep out of reach of children. In case of overdose, get medical help or contact a Poison Control Center right away.

Do not use if tamper evident seal is broken or missing. Store in a cool, dry place.

DOSAGE AND ADMINISTRATION

DIRECTIONS: Take two tablets twice a day under the tongue.

INACTIVE INGREDIENT

INACTIVE INGREDIENTS: Lactose, Magnesium stearate, Microcrystalline cellulose.

QUESTIONS

Manufactured for:

T-Gone Remedies

375 N. Stephanie St., STE 1411

Henderson, NV 89014-8909

Web: www.T-gone.com

Tel: 800-314-2910

customercare@t-gone.com

PACKAGE LABEL

T-Gone Remedies.

Type 4 Noise Max

HOMEOPATHIC

120 TABLETS